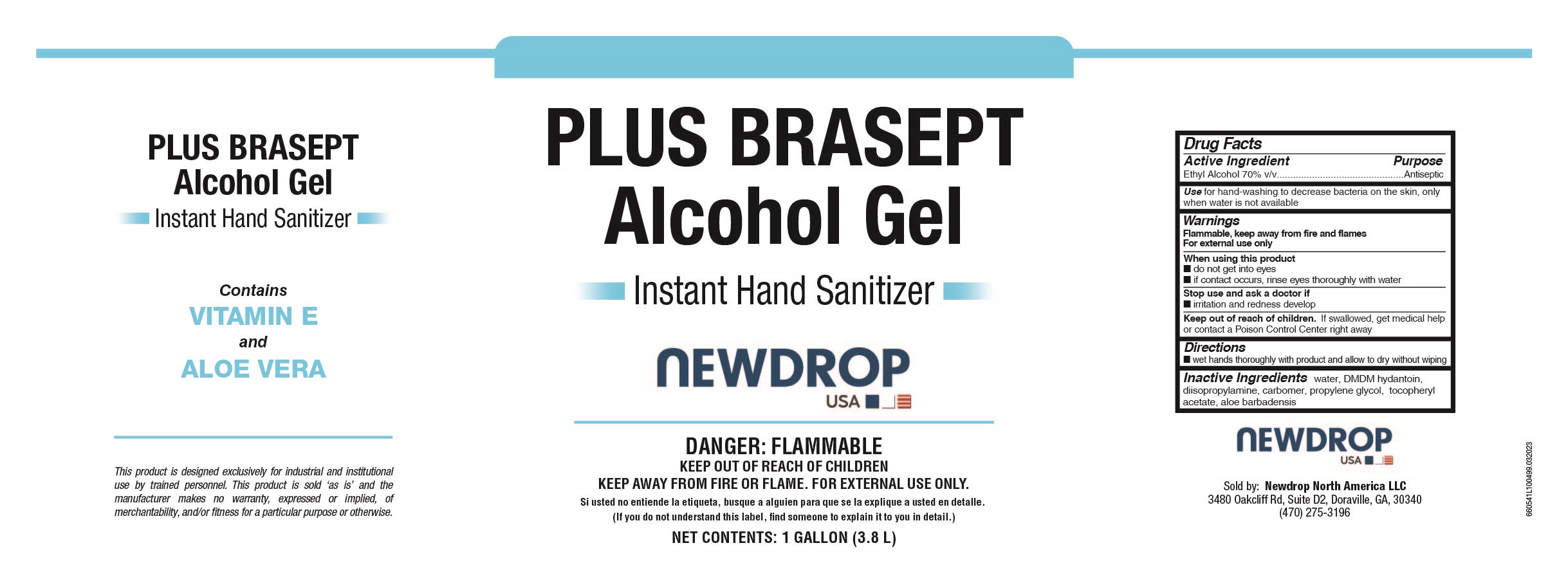 DRUG LABEL: Plus Brasept Alcocol Gel
NDC: 83318-605 | Form: GEL
Manufacturer: NEWDROP NORTH AMERICA LLC
Category: otc | Type: HUMAN OTC DRUG LABEL
Date: 20251120

ACTIVE INGREDIENTS: ALCOHOL 0.7 mL/1 mL
INACTIVE INGREDIENTS: WATER; CARBOMER 934; PROPYLENE GLYCOL; ALOE VERA LEAF; .ALPHA.-TOCOPHEROL ACETATE, DL-; DIISOPROPYLAMINE; DMDM HYDANTOIN

Plus Brasept Alcocol Gel 6605 Drug Facts and Label

Drug Facts Box OTC-Active Ingredient Section

Ethyl Alcohol 70% b/v

Drug Facts Box OTC-Purpose Section

Antiseptic

Drug Facts Box OTC-Indications & Usage Section

for hand-washing to decrease bacteria on the skin, only when water is not available

Drug Facts Box OTC-Warnings Section

FLAMMABLE, keep away from fire and flames

For external use only

Drug Facts Box OTC-When Using Section

do not get into eyes

if contact occurs, rinse eyes thoroughly with water

Drug Facts Box OTC-Stop Use Section

irritation and redness develop

Drug Facts Box OTC-Keep Out of Reach of Children Section

if swallowed, get medical help or contact a Poison Control Center right away

Drug Facts Box OTC-Dosage & Administration Section

wet hands thoroughly with product and allow to dry without wiping

Drug Facts Box OTC-Inactive Ingredient Section

water, DMD hydantoin, diisopropylamine, carbomer, propylene glycol, tocopheryl acetate, aloe barbadensis, fragrance